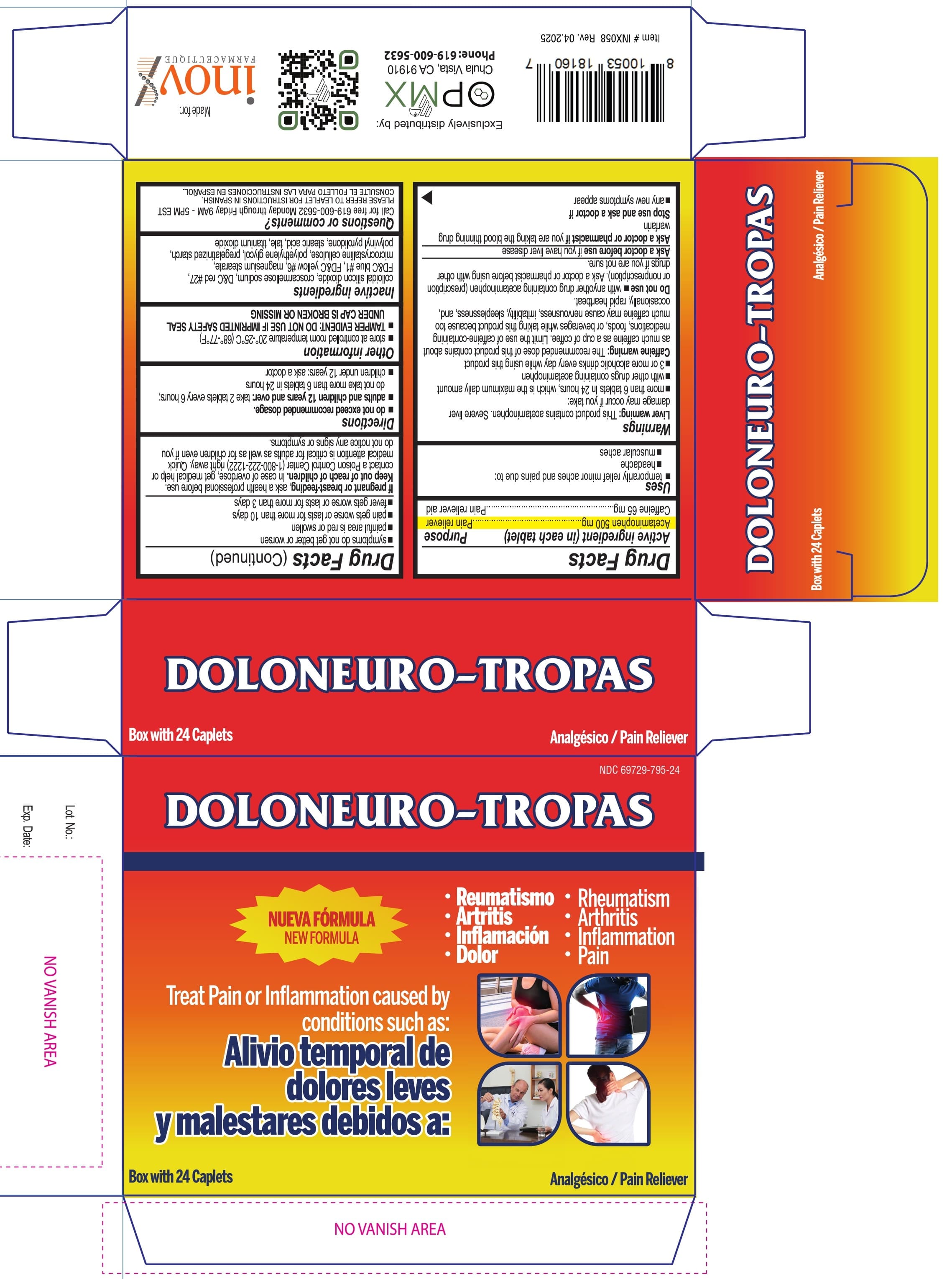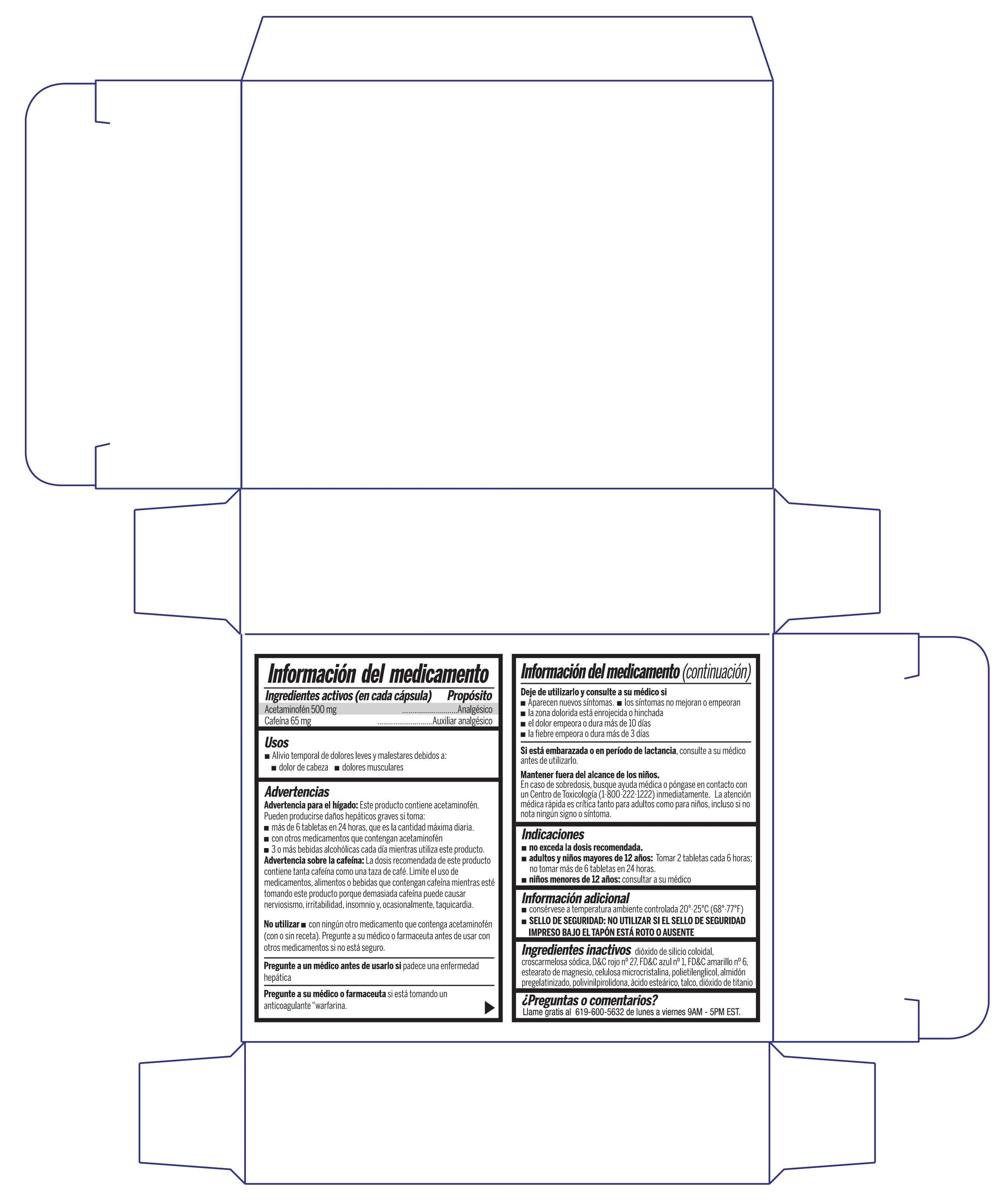 DRUG LABEL: DOLONEURO-TROPAS
NDC: 69729-795 | Form: TABLET, FILM COATED
Manufacturer: OPMX LLC
Category: otc | Type: HUMAN OTC DRUG LABEL
Date: 20250414

ACTIVE INGREDIENTS: ACETAMINOPHEN 500 mg/1 1; CAFFEINE 65 mg/1 1
INACTIVE INGREDIENTS: STARCH, CORN; POVIDONE, UNSPECIFIED; CROSCARMELLOSE SODIUM; FD&C BLUE NO. 1; FD&C YELLOW NO. 6; MAGNESIUM STEARATE; POLYETHYLENE GLYCOL, UNSPECIFIED; TITANIUM DIOXIDE; TALC; STEARIC ACID; D&C RED NO. 27; SILICON DIOXIDE; MICROCRYSTALLINE CELLULOSE

DoloNeuro Tropas

Active ingredients (in each caplet)

Acetaminophen 500 mg

Caffeine 65 mg

Purposes

Pain reliever

Pain reliever aid

Uses

- temporarily relieves minor aches and pain due to:
- headache
- muscular aches

Warnings

Liver warning

This product contains acetaminophen. Severe liver damage may occur if you take

- more than 6 caplets in 24 hours, which is the maximum daily amount
- with other drugs containing acetaminophen
- 3 or more alcoholic drinks every day while using this product

Caffeine warning

The recommended dose of this product contains about as much caffeine as a cup of coffee. Limit the use of caffeine-containing medications, foods, or beverages while taking this product because too much caffeine may cause nervousness, irritability, sleeplessness, and occasionally, rapid heartbeat.

Do not use

- with any other drug containing acetaminophen (prescription or nonprescription). Ask a doctor or pharmacist before using with other drugs if you are not sure.

Ask a doctor before use if

you have liver disease

Ask a doctor or pharmacist

if you are taking the blood thinning drug warfarin

Stop use and ask a doctor if

- any new symptoms occur
- symptoms do not get better or worsen
- painful area is red or swollen
- pain gets worse or lasts for more than 10 days
- fever gets worse or lasts for more than 3 days

If pregnant or breast-feeding,

ask a health professional before use.

Keep out of reach of children.

In case of overdose, get medical help or contact a Poison Control Center (1-800-222-1222) right away. Quick medical attention is critical for adults as well as for children even if you do not notice any signs or symptoms.

Directions

- do not exceed recommended dosage
- adults and children 12 years and over: take 2 caplets every 6 hours; do not take more than 6 caplets in 24 hours
- children under 12 years: ask a doctor

Other information

- store at controlled room temperature 20°-25°C (68°-77°F)
- TAMPER EVIDENT: DO NOT USE IF IMPRINTED SAFETY SEAL UNDER CAP IS BROKEN OR MISSING

Inactive ingredients

colloidal silicon dioxide, croscarmellose sodium, D&C red #27, FD&C blue #1, FD&C yellow #6, magnesium stearate, microcrystalline cellulose, polyethylene glycol, pregelatinized starch, polyvinylpyrrolidone, stearic acid, talc, titanium dioxide.

Questions or comments?

Call toll free 1-844-832-1138 Monday through Friday 9AM - 5PM EST

PLEASE REFER TO LEAFLET FOR INSTRUCTIONS IN SPANISH.

CONSULTE EL FOLLETO PARA LAS INSTRUCCIONES EN ESPAÑOL.

Principal Display Panel

NDC 69729-795-24

DOLONEURO-TROPAS

NUEVA FÓRMULA

NEW FORMULA

Treat Pain of Inflammation caused by conditions such as:

Alivio temporal de dolores leves y malestares debidos a:

Reumatismo, Artritis, Inflamación, Dolor

Rheumatism, Arthritis, Inflammation, Pain

Box with 24 Caplets

Analgésico/Pain Reliever

Exclusively distributed by:

OPMX

Chula Vista, CA 91910

Phone:619-600-5632